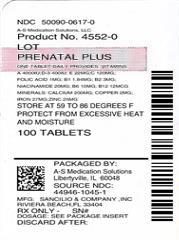 DRUG LABEL: PNV Prenatal Plus Multivitamin
NDC: 50090-0617 | Form: TABLET
Manufacturer: A-S Medication Solutions
Category: prescription | Type: HUMAN PRESCRIPTION DRUG LABEL
Date: 20171023

ACTIVE INGREDIENTS: VITAMIN A ACETATE 2000 [iU]/1 1; .BETA.-CAROTENE 2000 [iU]/1 1; ASCORBIC ACID 120 mg/1 1; CHOLECALCIFEROL 400 [iU]/1 1; .ALPHA.-TOCOPHEROL ACETATE, DL- 22 mg/1 1; THIAMINE MONONITRATE 1.84 mg/1 1; RIBOFLAVIN 3 mg/1 1; NIACINAMIDE 20 mg/1 1; PYRIDOXINE HYDROCHLORIDE 10 mg/1 1; FOLIC ACID 1 mg/1 1; CYANOCOBALAMIN 12 ug/1 1; CALCIUM CARBONATE 200 mg/1 1; FERROUS FUMARATE 27 mg/1 1; ZINC OXIDE 25 mg/1 1; CUPRIC OXIDE 2 mg/1 1
INACTIVE INGREDIENTS: CROSCARMELLOSE SODIUM; MICROCRYSTALLINE CELLULOSE; TALC; MAGNESIUM STEARATE

PNV Prenatal Plus MULTIVITAMIN Tablets

DESCRIPTION

Each PNV Tablet Contains: | Amount Per Serving
Vitamin A (from Acetate and Beta Carotene) | 4000 I.U.
Vitamin C (Ascorbic Acid) | 120 mg
Vitamin D-3 (Cholecalciferol) | 400 I.U.
Vitamin E (dl-Alpha Tocopheryl Acetate) | 22 mg
Vitamin B-1 (from Thiamine Mononitrate) | 1.84 mg
Vitamin B-2 (Riboflavin) | 3 mg
Niacin (as Niacinamide) | 20 mg
Vitamin B-6 (from Pyridoxine HCl) | 10 mg
Folic Acid | 1 mg
Vitamin B-12 (Cyanocobalamin) | 12 mcg
MINERALS:
Calcium (as Calcium Carbonate) | 200 mg
Iron (from Ferrous Fumarate) | 27 mg
Zinc (from Zinc Oxide) | 25 mg
Copper (from Cupric Oxide) | 2 mg

Other Ingredients: Croscarmellose Sodium, Microcrystalline Cellulose, Talc, Magnesium Stearate.

Indications

To provide Vitamin and Mineral supplementation throughout pregnancy and during the postnatal period for both the lactating and non-lactating mother. It is also useful for improving nutritional status prior to conception.

Dosage

As a dietary adjunct before, during and after pregnancy, take one tablet daily with a meal, or as directed by a physician.

WARNING

Accidental overdose of iron-containing products is a leading cause of fatal poisoning in children under 6. Keep this product out of the reach of children. In case of accidental overdose, call a doctor or poison control center immediately.

Precautions

Folic Acid may mask the symptoms of hematological damage due to Vitamin B12 deficiency of pernicious anemia while the associated neurological damage progresses.

STORAGE AND HANDLING

STORE AT CONTROLLED ROOM TEMPERATURE 15°-30°C (59°-86°F). AVOID EXCESS HEAT. Dispense in a well closed light-resistant container, with a child resistant cap.

This medical food product is formulated to be administered orally, under the supervision of a physician.

KEEP THIS AND ALL MEDICATIONS OUT OF THE REACH OF CHILDREN.

Manufactured by:
Sancilio & Company, Inc.
3874 Fiscal Court
Riviera Beach, FL 33404
(800)SCI-8711

REV: 04/11/13

HOW SUPPLIED

Product: 50090-0617

NDC: 50090-0617-0 100 TABLET in a BOTTLE, PLASTIC

NDC: 50090-0617-1 30 TABLET in a BOTTLE